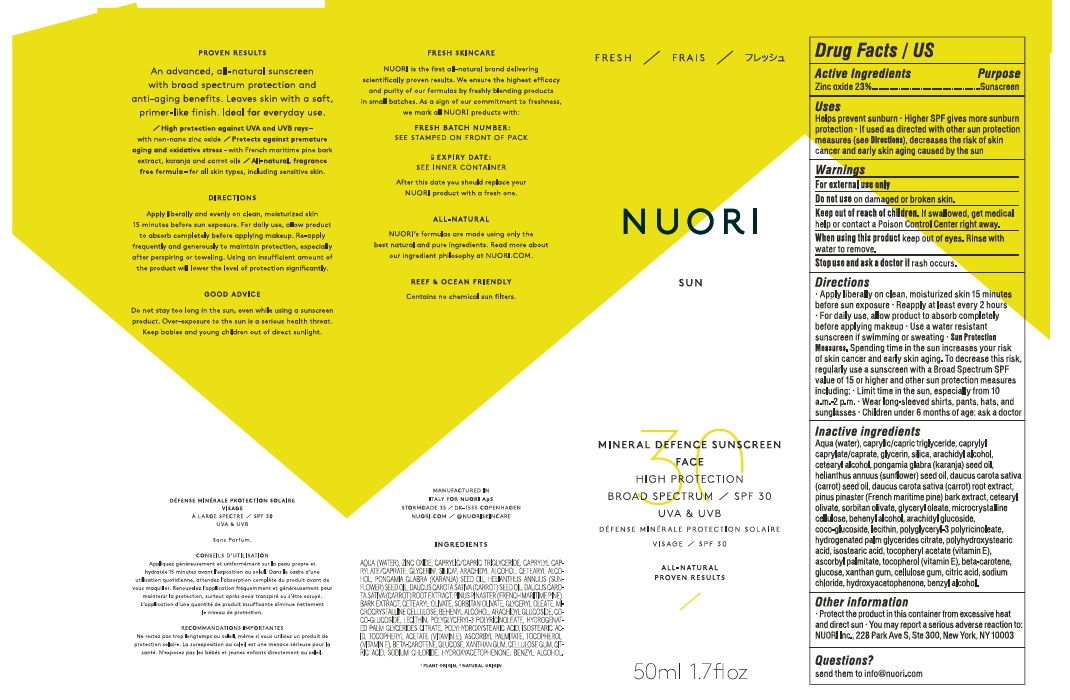 DRUG LABEL: NUORI MINERAL DEFENCE SUNSCREEN SPF 30
NDC: 72894-003 | Form: CREAM
Manufacturer: NUORI ApS
Category: otc | Type: HUMAN OTC DRUG LABEL
Date: 20241205

ACTIVE INGREDIENTS: ZINC OXIDE 230 mg/1 mL
INACTIVE INGREDIENTS: MEDIUM-CHAIN TRIGLYCERIDES; ISOSTEARIC ACID; ANHYDROUS DEXTROSE; XANTHAN GUM; CARBOXYMETHYLCELLULOSE SODIUM; CITRIC ACID MONOHYDRATE; SILICON DIOXIDE; KARUM SEED OIL; SORBITAN OLIVATE; DOCOSANOL; ARACHIDYL GLUCOSIDE; SUNFLOWER OIL; CARROT SEED OIL; GLYCERYL MONOOLEATE; .ALPHA.-TOCOPHEROL ACETATE; HYDROXYACETOPHENONE; BENZYL ALCOHOL; TOCOPHEROL; MARITIME PINE; BETA CAROTENE; SODIUM CHLORIDE; WATER; CAPRYLYL CAPRYLATE/CAPRATE; ARACHIDYL ALCOHOL; CARROT; CETOSTEARYL ALCOHOL; CETEARYL OLIVATE; MICROCRYSTALLINE CELLULOSE; COCO GLUCOSIDE; POLYHYDROXYSTEARIC ACID (2300 MW); ASCORBYL PALMITATE; GLYCERIN

NUORI MINERAL DEFENCE SUNSCREEN SPF 30

Active Ingredients

Zinc Oxide 23%

Purpose: Sunscreen

Purpose

Sunscreen

Uses

- Helps prevent sunburn
- Higher SPF gives more sunburn protection
- If used as directed with other sun protection measures (see Directions), decreases the risk of skin cancer and early skin aging caused by the sun

Warnings

For external use only

Do not use on damaged or broken skin.

KEEP OUT OF REACH OF CHILDREN

Keep out of the reach of children. If swallowed, get medical help or contact a Poison Control Center right away.

When using this product keep out of eyes. Rinse with water to remove.

Stop use and ask a doctor if rash occurs.

Directions

- Apply liberally on clean, moisturized skin 15 minutes before sun exposure.
- Reapply at least every 2 hours.
- For daily use, allow product to absorb completely before applying makeup.
- Use a water resistant sunscreen if swimming or sweating.
- Sun Protection Measures. Spending time in the sun increases your risk of skin cancer and early skin aging. To decrease this risk, regularly use a sunscreen with a Broad Spectrum SPF value of 15 or higher and other sun protection measures including:
- Limit time in the sun, especially from 10 a.m.-2 p.m.
- Wear long-sleeved shirts, pants, hats and sunglasses.

- Children under 6 months of age: ask a doctor.

Inactive ingredients

Aqua (water), caprylic/capric triglyceride, caprylyl caprylate/caprate, glycerin, silica, arachidyl alcohol, cetearyl alcohol, pongamia glabra (karanja) seed oil, helianthus annuus (sunflower) seed oil, daucus carota sativa (carrot) seed oil, daucus carota sativa (carrot) root extract, pinus pinaster (french maritime pine) bark extract, cetearyl olivate, sorbitan olivate, glyceryl oleate, microcrystalline cellulose, behenyl alcohol, arachidyl glucoside, coco-glucoside, lecithin, polyglyceryl-3 polyricinoleate, hydrogenated palm glycerides citrate, polyhydroxystearic acid, isostearic acid, tocopheryl acetate (vitamin e), ascorbyl palmitate, tocopherol (vitamin e), beta-carotene, glucose, xanthan gum, cellulose gum, citric acid, sodium chloride, hydroxyacetophenone, benzyl alcohol.

Other information

- Protect the product in this container from excessive heat and direct sun
- You may report a serious adverse reaction to: NUORI Inc., 228 Park Ave S, Ste 300, New York, NY 10003

Questions?

send them to info@nuori.com

Company Information

MANUFACTURED IN ITALY FOR NUORI ApS

STORMGADE 35/ DK-1555 COPENHAGEN

NUORI.COM/ @NUORISKINCARE

Product Packaging

NUORI

SUN

MINERAL DEFENCE SUNSCREEN

FACE

HIGH PROTECTION

BROAD SPECTRUM SPF 30

UVA & UVB

ALL-NATURAL

PROVEN RESULTS

50ml 1.7floz